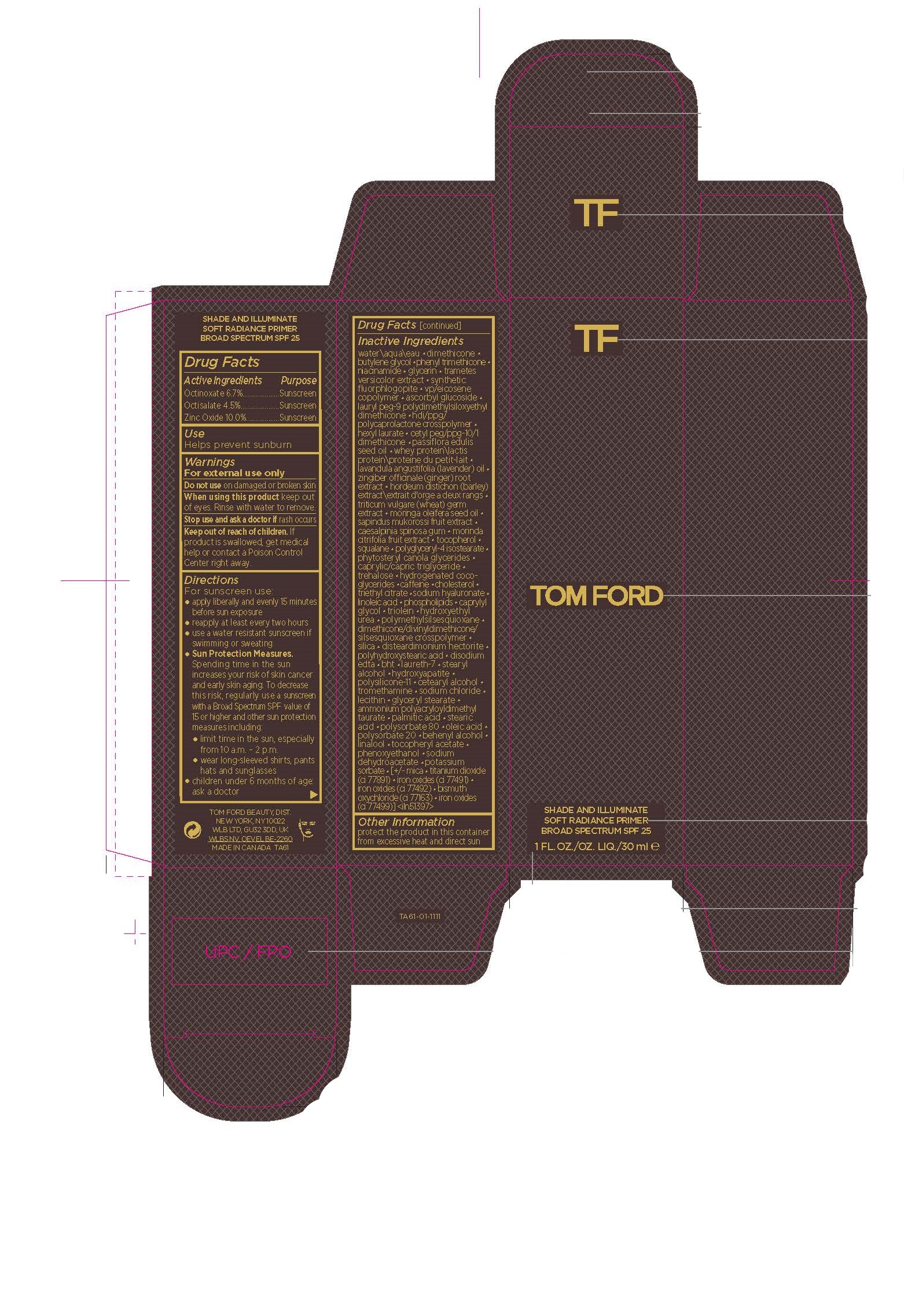 DRUG LABEL: SHADE and ILLUMINATE SOFT RAD PRMR SPF
NDC: 76398-013 | Form: CREAM
Manufacturer: TOM FORD BEAUTY DIST
Category: otc | Type: HUMAN OTC DRUG LABEL
Date: 20231201

ACTIVE INGREDIENTS: ZINC OXIDE 100 mg/1 mL; OCTINOXATE 67 mg/1 mL; OCTISALATE 45 mg/1 mL
INACTIVE INGREDIENTS: TREHALOSE; CAFFEINE; CHOLESTEROL; MORINGA OLEIFERA SEED OIL; SAPINDUS MUKOROSSI FRUIT; CAESALPINIA SPINOSA RESIN; MORINDA CITRIFOLIA FRUIT; POLYGLYCERYL-4 ISOSTEARATE; TRAMETES VERSICOLOR FRUITING BODY; LAURYL PEG-9 POLYDIMETHYLSILOXYETHYL DIMETHICONE; OLEIC ACID; POLYSORBATE 20; .ALPHA.-TOCOPHEROL ACETATE; MICA; FERROSOFERRIC OXIDE; LECITHIN, SOYBEAN; LAVENDER OIL; LINOLEIC ACID; STEARYL ALCOHOL; PHENOXYETHANOL; POTASSIUM SORBATE; HEXYL LAURATE; GINGER; MEDIUM-CHAIN TRIGLYCERIDES; HYDROGENATED COCO-GLYCERIDES; TRIETHYL CITRATE; SILICON DIOXIDE; POLYHYDROXYSTEARIC ACID (2300 MW); BUTYLATED HYDROXYTOLUENE; CETOSTEARYL ALCOHOL; MAGNESIUM POTASSIUM ALUMINOSILICATE FLUORIDE; TITANIUM DIOXIDE; SQUALANE; HYALURONATE SODIUM; DISTEARDIMONIUM HECTORITE; SODIUM DEHYDROACETATE; BISMUTH OXYCHLORIDE; WATER; DIMETHICONE; CETYL PEG/PPG-10/1 DIMETHICONE (HLB 5); PASSIFLORA EDULIS SEED OIL; WHEY; BARLEY; WHEAT GERM; TOCOPHEROL; FERRIC OXIDE RED; FERRIC OXIDE YELLOW; CAPRYLYL GLYCOL; GLYCERYL TRIOLEATE; HYDROXYETHYL UREA; POLYMETHYLSILSESQUIOXANE (4.5 MICRONS); DIMETHICONE/DIVINYLDIMETHICONE/SILSESQUIOXANE CROSSPOLYMER; EDETATE DISODIUM ANHYDROUS; LAURETH-7; TRIBASIC CALCIUM PHOSPHATE; DIMETHICONE/VINYL DIMETHICONE CROSSPOLYMER (SOFT PARTICLE); TROMETHAMINE; SODIUM CHLORIDE; GLYCERYL MONOSTEARATE; AMMONIUM POLYACRYLOYLDIMETHYL TAURATE (55000 MPA.S); PALMITIC ACID; STEARIC ACID; POLYSORBATE 80; DOCOSANOL; LINALOOL, (+/-)-; BUTYLENE GLYCOL; PHENYL TRIMETHICONE; NIACINAMIDE; GLYCERIN; EICOSYL POVIDONE; ASCORBYL GLUCOSIDE

SHADE AND ILLUMINATE SOFT RAD PRMR SPF

Active Ingredients

Octinoxate 6.7%

Octisalate 4.5%

Zinc Oxide 10.0%

Purpose

Sunscreen

USE

Helps prevent sunburn

Warnings

For external use only

Do not use

on damaged or broken skin

When using this product

keep out of eyes. Rinse with water to remove

Stop use and ask a doctor if

rash occurs

Keep out of reach of children

If product is swallowed, get medical
help or contact a Poison Control
Center right away.

Directions

For sunscreen use:
• apply liberally and evenly 15 minutes
before sun exposure
• reapply at least every two hours
• use a water resistant sunscreen if
swimming or sweating
• Sun Protection Measures.
Spending time in the sun
increases your risk of skin cancer
and early skin aging. To decrease
this risk, regularly use a sunscreen
with a Broad Spectrum SPF value of
15 or higher and other sun protection
measures including:
• limit time in the sun, especially
from 10 a.m. – 2 p.m.
• wear long-sleeved shirts, pants
hats and sunglasses
• children under 6 months of age:
ask a doctor

Inactive Ingredients

WATER\AQUA\EAU [] DIMETHICONE [] BUTYLENE GLYCOL [] PHENYL TRIMETHICONE [] NIACINAMIDE [] GLYCERIN [] TRAMETES VERSICOLOR EXTRACT [] SYNTHETIC FLUORPHLOGOPITE [] VP/EICOSENE COPOLYMER [] ASCORBYL GLUCOSIDE [] LAURYL PEG-9 POLYDIMETHYLSILOXYETHYL DIMETHICONE [] HDI/PPG/POLYCAPROLACTONE CROSSPOLYMER [] HEXYL LAURATE [] CETYL PEG/PPG-10/1 DIMETHICONE [] PASSIFLORA EDULIS SEED OIL [] WHEY PROTEIN\LACTIS PROTEIN\PROTEINE DU PETIT-LAIT [] LAVANDULA ANGUSTIFOLIA (LAVENDER) OIL [] ZINGIBER OFFICINALE (GINGER) ROOT EXTRACT [] HORDEUM DISTICHON (BARLEY) EXTRACT\EXTRAIT D'ORGE A DEUX RANGS [] TRITICUM VULGARE (WHEAT) GERM EXTRACT [] MORINGA OLEIFERA SEED OIL [] SAPINDUS MUKOROSSI FRUIT EXTRACT [] CAESALPINIA SPINOSA GUM [] MORINDA CITRIFOLIA FRUIT EXTRACT [] TOCOPHEROL [] SQUALANE [] POLYGLYCERYL-4 ISOSTEARATE [] PHYTOSTERYL CANOLA GLYCERIDES [] CAPRYLIC/CAPRIC TRIGLYCERIDE [] TREHALOSE [] HYDROGENATED COCO-GLYCERIDES [] CAFFEINE [] CHOLESTEROL [] TRIETHYL CITRATE [] SODIUM HYALURONATE [] LINOLEIC ACID [] PHOSPHOLIPIDS [] CAPRYLYL GLYCOL [] TRIOLEIN [] HYDROXYETHYL UREA [] POLYMETHYLSILSESQUIOXANE [] DIMETHICONE/DIVINYLDIMETHICONE/SILSESQUIOXANE CROSSPOLYMER [] SILICA [] DISTEARDIMONIUM HECTORITE [] POLYHYDROXYSTEARIC ACID [] DISODIUM EDTA [] BHT [] LAURETH-7 [] STEARYL ALCOHOL [] HYDROXYAPATITE [] POLYSILICONE-11 [] CETEARYL ALCOHOL [] TROMETHAMINE [] SODIUM CHLORIDE [] LECITHIN [] GLYCERYL STEARATE [] AMMONIUM POLYACRYLOYLDIMETHYL TAURATE [] PALMITIC ACID [] STEARIC ACID [] POLYSORBATE 80 [] OLEIC ACID [] POLYSORBATE 20 [] BEHENYL ALCOHOL [] LINALOOL [] TOCOPHERYL ACETATE [] PHENOXYETHANOL [] SODIUM DEHYDROACETATE [] POTASSIUM SORBATE [] [+/- MICA [] TITANIUM DIOXIDE (CI 77891) [] IRON OXIDES (CI 77491) [] IRON OXIDES (CI 77492) [] BISMUTH OXYCHLORIDE (CI 77163) [] IRON OXIDES (CI 77499)] <ILN51397>

Other Information

protect the product in this container
from excessive heat and direct sun

PRINCIPAL DISPLAY PANEL

TOM FORD

SHADE AND ILLUMINATE
SOFT RADIANCE PRIMER
BROAD SPECTRUM SPF 25
1 FL. OZ./OZ. LIQ./30 ml ℮